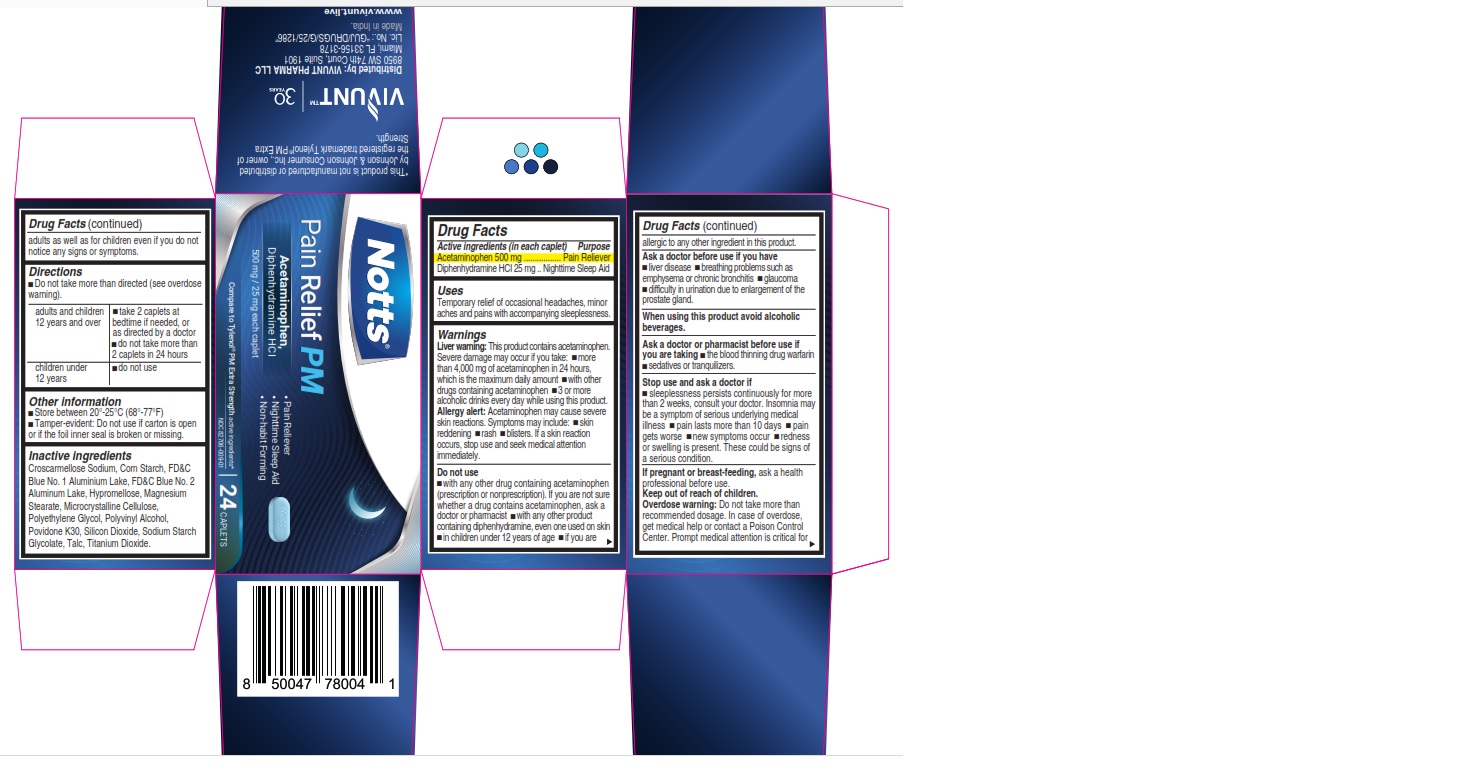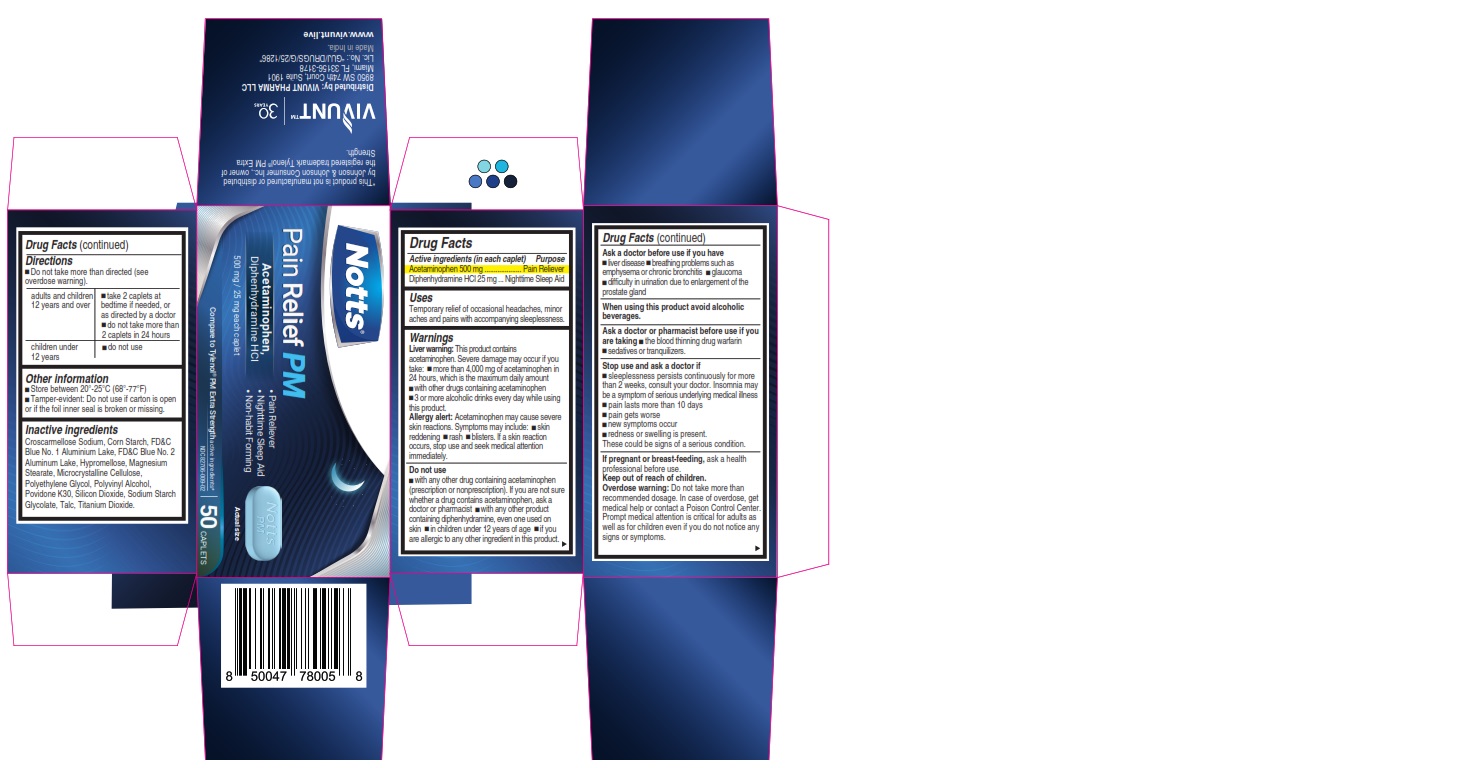 DRUG LABEL: NOTTS - Pain Relief PM
NDC: 82706-009 | Form: TABLET
Manufacturer: VIVUNT PHARMA LLC
Category: otc | Type: HUMAN OTC DRUG LABEL
Date: 20241202

ACTIVE INGREDIENTS: ACETAMINOPHEN 500 mg/1 1; DIPHENHYDRAMINE HYDROCHLORIDE 25 mg/1 1
INACTIVE INGREDIENTS: FD&C BLUE NO. 2; HYPROMELLOSE, UNSPECIFIED; MAGNESIUM STEARATE; MICROCRYSTALLINE CELLULOSE; POLYETHYLENE GLYCOL, UNSPECIFIED; TITANIUM DIOXIDE; STEARIC ACID; POVIDONE; SODIUM STARCH GLYCOLATE TYPE A; STARCH, CORN

NOTTS - Pain Relief PM

Drug Facts

ACTIVE INGREDIENT

Active ingredients (in each caplet) | Purpose
Acetaminophen 500 mg | Pain Reliever
Diphenhydramine HCl 25 mg | Nighttime Sleep Aid

Uses

Temporary relief of occasional headaches, minor aches and pains with accompanying sleeplessness

Warnings

Liver Warning

This product contains acetaminophen. Severe liver damage may occur if you take

- more than 4,000 mg of acetaminophen in 24 hours, which is the maximum daily amount.
- with other drugs containing acetaminophen
- 3 or more alcoholic drinks every day while using this product

Allergy Alert

Acetaminophen may cause severe skin reactions. Symptoms may include:

- skin reddening
- rash
- blisters

If a skin reaction occurs, stop use and seek medical attention immediately.

Do not use

- with any other drug containing acetaminophen (prescription or nonprescription). If you are not sure whether a drug contains acetaminophen, ask a doctor or pharmacist.
- with any other product containing diphenhydramine, even one used on skin
- in children under 12 years of age
- if you are allergic to any other ingredient in this product.

Ask a doctor before use if you have

- liver disease
- breathing problems such as emphysema or chronic bronchitis
- glaucoma
- difficulty in urinatation due to enlargement of the prostate gland

When using this product

avoid alcoholic drinks

Ask a doctor or pharmacist before use if you are taking

- the blood thinning drug warfarin
- sedatives or tranquilizers

Stop use and ask a doctor if

- sleeplessness persists continuously for more than 2 weeks, consult your doctor. Insomnia may be a symptom of serious underlying medical illness.
- pain lasts more than 10 days
- pain gets worse
- new symptoms occur
- redness or swelling is present.

These could be signs of a serious condition.

If pregnant or breast-feeding,

ask a health professional before use.

Keep out of reach of children.

Overdose warning

Do not take more the recommended dosage. In case of overdose, get medical help or contact a Poison Control Center. Prompt medical attention is critical for adults as well as for children even if you do not notice any signs or symptoms.

Directions

- Do not take more than directed (see overdose warning)

adults and children 12 years and over | - take 2 caplets at bedtime if needed, or as directed by a doctor. - do not take more than 2 caplets in 24 hours
children under 12 years | do not use

Other information

- Store between 20-25°C (68-77°F)
- Tamper-evident: Do not use if carton is open or if the foil inner seal is broken or missing.

Inactive ingredients

Croscarmellose Sodium, Corn Starch, FD&C Blue No. 1 Aluminium Lake, FD&C Blue No. 2 Aluminium Lake, Hypromellose, Magnesium Stearate, Microcrystalline Cellulose, Polyethylene Glycol, Polyvinyl Alcohol, Povidone K30, Silicon Dioxide, Sodium Starch Glycolate, Talc, Titanium Dioxide.

*This product is not manufactured or distributed by Johnson & Johnson Consumer Inc., owner of the registered trademark Tylenol ® Extra Strength PM.

Distributed by:

VIVUNT PHARMA LLC

8950 SW 74th Court, Suite 1901

Miami, Florida FL 33156-3178

Made in India

PRINCIPAL DISPLAY PANEL - 24 Caplets

NOTTS™

Pain Relief PM

Acetaminophen,

Diphenhydramine HCl

500 mg/ 25 mg each caplet

Pain Reliever
Nighttime Sleep Aid
Non-habit Forming

Compare to Tylenol® Extra Strength PM active ingredients*

NDC 82706-009-01

24 CAPLETS

PRINCIPAL DISPLAY PANEL - 50 Caplets

NOTTS™

Pain Relief PM

Acetaminophen,

Diphenhydramine HCl

500 mg/ 25 mg each caplet

- Pain Reliever
- Nighttime Sleep Aid
- Non-habit Forming

Compare to Tylenol® Extra Strength PM active ingredients*

NDC 82706-009-02

50 CAPLETS